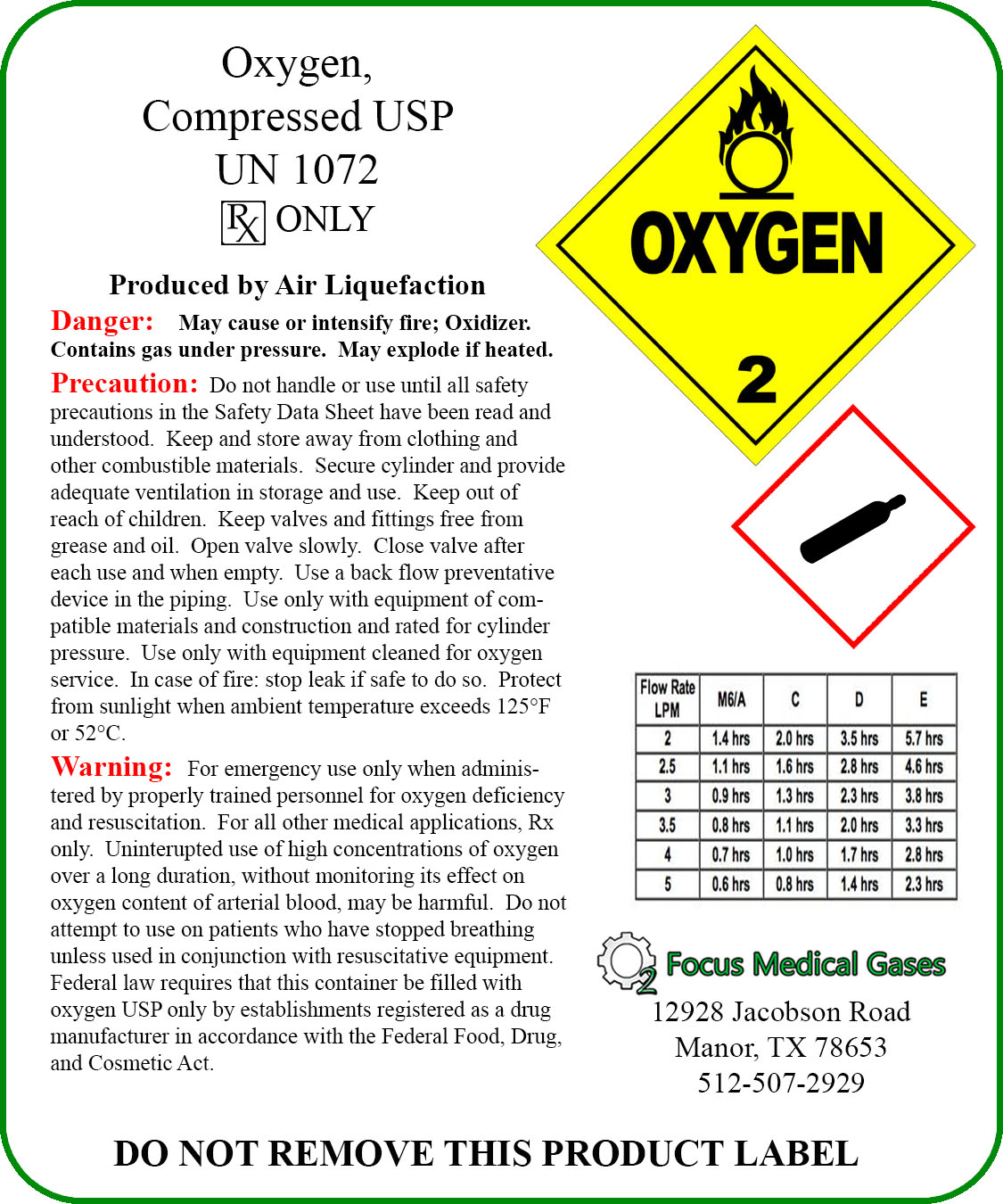 DRUG LABEL: Focus Medical Oxygen
NDC: 70291-1000 | Form: GAS
Manufacturer: Focus Medical Gases LLC
Category: prescription | Type: HUMAN PRESCRIPTION DRUG LABEL
Date: 20160224

ACTIVE INGREDIENTS: OXYGEN 1 L/1 L

Focus Medical Oxygen